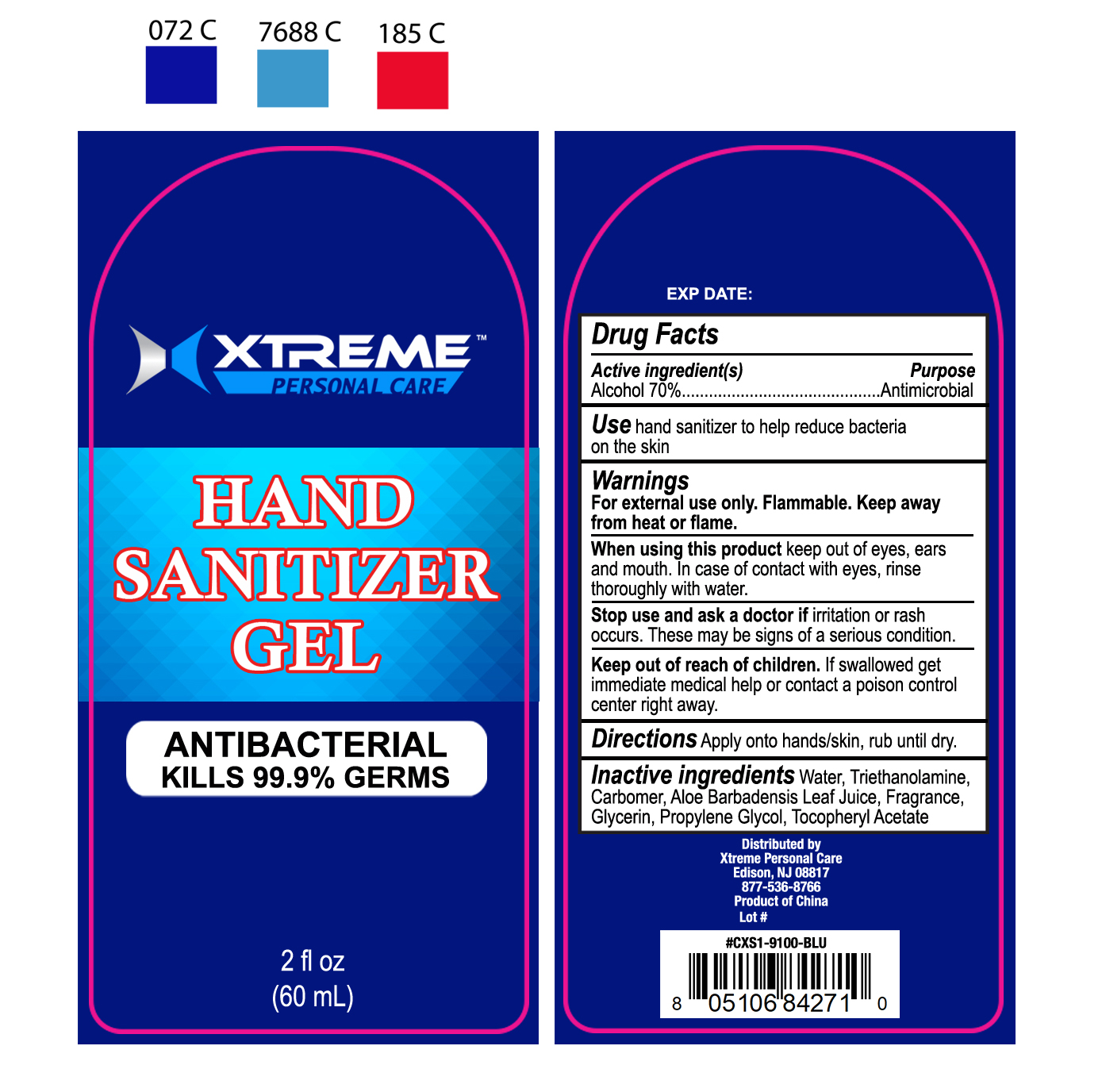 DRUG LABEL: XTREME Personal Care Hand Sanitizer
NDC: 52989-004 | Form: GEL
Manufacturer: Taizhou Yadai Daily-Use Co., Ltd.
Category: otc | Type: HUMAN OTC DRUG LABEL
Date: 20200619

ACTIVE INGREDIENTS: ALCOHOL 70 mL/100 mL
INACTIVE INGREDIENTS: GLYCERIN; CARBOMER 934; TROLAMINE; PROPYLENE GLYCOL; ALOE VERA LEAF; .ALPHA.-TOCOPHEROL ACETATE

52989-004

Active Ingredient(s)

Ethyl Alcohol 70% v/v

Purpose

Antimicrobial

Use

Hand sanitizer to help decrease bacteria on the skin

Warnings

For external use only. Flammable. Keep away from heat or flame

When using this product, keep out of eyes, ears or mouth. In case of contact with eyes, rinse thoroughly with water.

Stop use and ask a doctor if irritation or rash occurs, these may be signs of serious condition.

Keep out of reach of children. If swallowed, get immediate medical help or contact a Poison Control Center right away.

Directions

- Apply onto hands/skin, rub until dry

Inactive ingredients

Water, Triethanolamine, Carbomer, Aloe Barbadensis Leaf Juice, Glycerin, Frangrance, Propylene Glycol, Tocopheryl Acetate